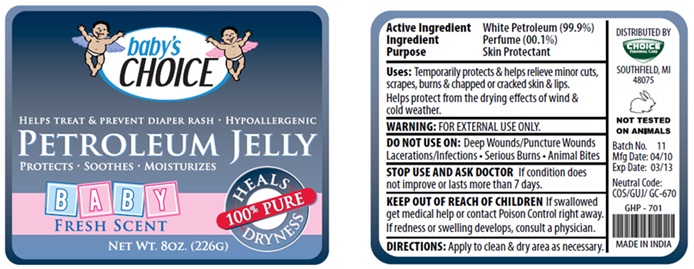 DRUG LABEL: Petroleum Jelly
NDC: 52862-003 | Form: JELLY
Manufacturer: International Wholesale Inc.
Category: otc | Type: HUMAN OTC DRUG LABEL
Date: 20101021

ACTIVE INGREDIENTS: PETROLATUM 99.9 g/100 g

Active Ingredient White Petroleum (99.9%)

Ingredient Perfume (0.1%)

Purpose Skin Protectant

INDICATIONS AND USAGE

Uses : Temporarily protects & helps relieve minor cuts, scrapes, burns & chapped or cracked skin & lips.

Helps protect from the drying effects of wind & cold weather.

WARNINGS

WARNING: FOR EXTERNAL USE ONLY

DO NOT USE ON: Deep Wounds/Puncture Wounds Lacerations/Infections . Serious Burns . Animal Bites

STOP USE AND ASK DOCTOR If condition does not improve or lasts more than 7 days.

KEEP OUT OF REACH OF CHILDREN If swallowed get medical help or contact Poison Control right away. If redness or swelling develops, consult a physician

DOSAGE AND ADMINISTRATION

DIRECTIONS: Apply to clean & dry area as necessary.